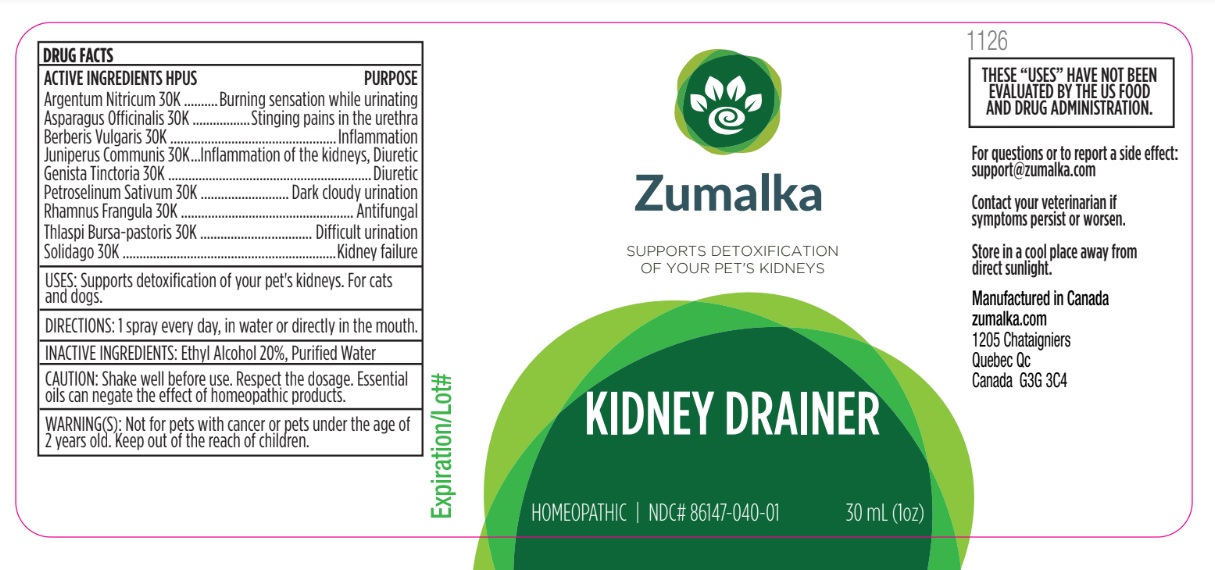 DRUG LABEL: KIDNEY DRAINER
NDC: 86147-040 | Form: LIQUID
Manufacturer: Groupe Cyrenne Inc.
Category: homeopathic | Type: OTC ANIMAL DRUG LABEL
Date: 20251120

ACTIVE INGREDIENTS: SILVER 30 [kp_C]/30 mL; ASPARAGUS 30 [kp_C]/30 mL; BERBERIS VULGARIS ROOT BARK 30 [kp_C]/30 mL; GENISTA TINCTORIA WHOLE 30 [kp_C]/30 mL; JUNIPER BERRY 30 [kp_C]/30 mL; PETROSELINUM CRISPUM WHOLE 30 [kp_C]/30 mL; FRANGULA ALNUS BARK 30 [kp_C]/30 mL; CAPSELLA BURSA-PASTORIS WHOLE 30 [kp_C]/30 mL; SOLIDAGO VIRGAUREA FLOWERING TOP 30 [kp_C]/30 mL
INACTIVE INGREDIENTS: ALCOHOL; WATER

Active ingredients Purpose

Argentum Nitricum 30k Burning sensation while urinating

Asparagus Officinalis 30k Stinging pains in the urethra

Berberis Vulgaris 30k Inflammation

Genista Tinctoria 30k Diuretic

Juniperus Communis 30k Inflammation of the kidneys, Diuretic

Petroselinum Sativum 30k Dark cloudy urination

Rhamnus Frangula 30k Antifungal

Thlaspi Bursa-pastoris 30k Difficult urination

Solidago 30k Kidney failure

Uses

Supports detoxification of your pet's kidneys. For cats and dogs.

Warnings

Keep out of reach of children. Not for pets with cancer or young pets under the age of 2 years old.

Direction

1 spray every day, in water or directly in the mouth.

Inactive ingredients

Ethyl alcohol 20%, purified water

Cautions

Shake well before use. Respect the dosage. Essential oils can negate the effects of homeopathic products. Store in a cool place away from direct sunlight.